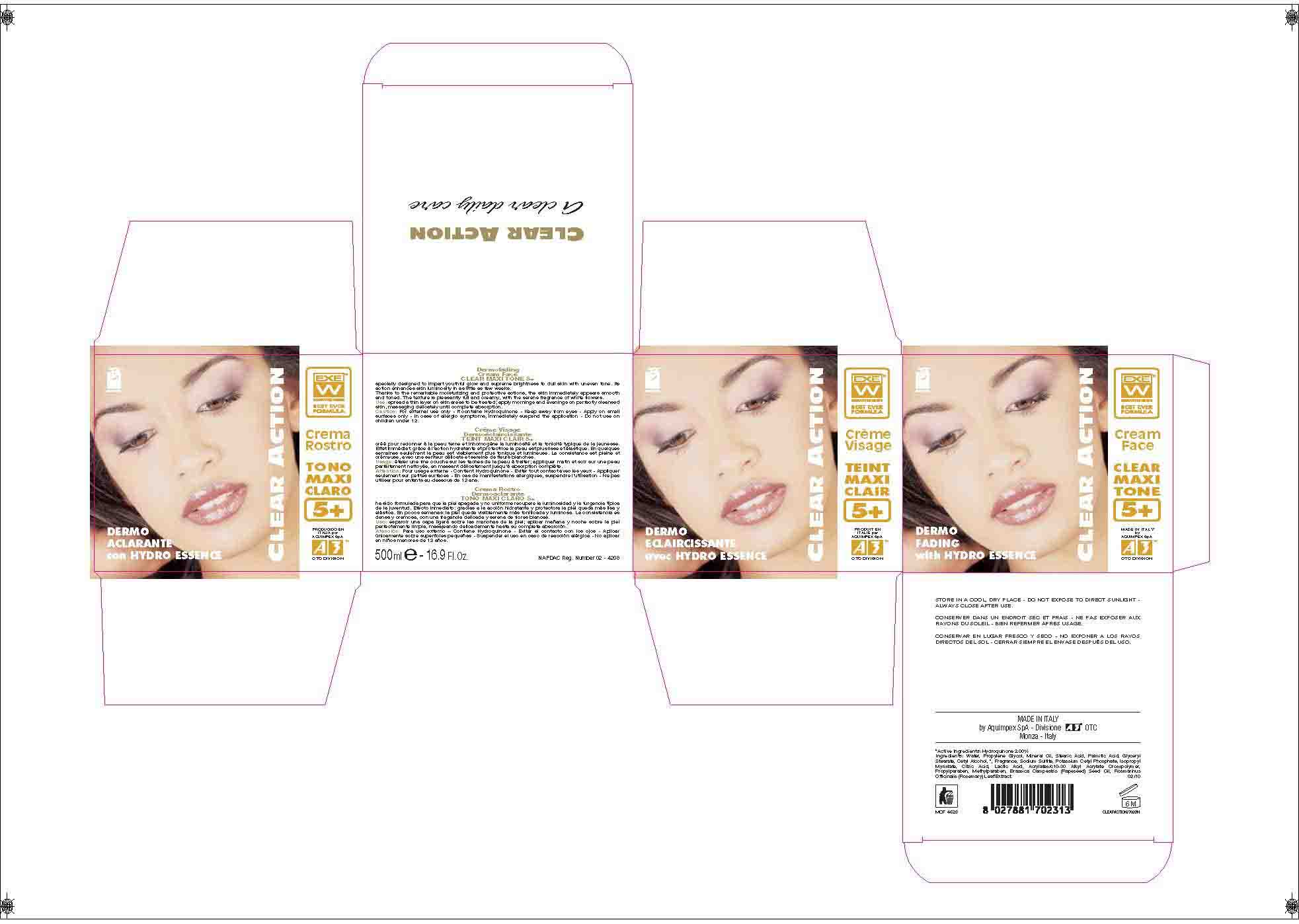 DRUG LABEL: CLEAR ACTION
NDC: 66273-0003 | Form: CREAM
Manufacturer: AQUIMPEX SPA
Category: otc | Type: HUMAN OTC DRUG LABEL
Date: 20110719

ACTIVE INGREDIENTS: HYDROQUINONE 10 mL/500 mL
INACTIVE INGREDIENTS: WATER; ROSEMARY; METHYLPARABEN; PROPYLENE GLYCOL; CARBOMER 934; CETYL ALCOHOL; STEARIC ACID; PALMITIC ACID; GLYCERYL MONOSTEARATE; ISOPROPYL MYRISTATE; MINERAL OIL; POTASSIUM CETYL PHOSPHATE; PROPYLPARABEN; CITRIC ACID MONOHYDRATE; LACTIC ACID; SODIUM SULFITE; BRASSICA RAPA VAR. RAPA OIL

Clear Action Dermofading Face Cream Maxi Tone 5+

PURPOSE

Dermofading Cream Face CLEAR MAXI TONE 5+ specially designed to impart youthful glow and supreme brightness to dull skin with uneven tone. Its action enhances skin luminosity in
as little as few weeks.

Use

Use: spread a thin layer on skin areas to be treated; apply mornings and evenings on perfectly cleansed skin, massaging delicately until complete absorption.

Caution

Caution: For external use only - It contains Hydroquinone - Keep away from eyes - Apply on small surfaces only - In case of allergic symptoms, immediately suspend the application - Do not use on children under 12.

Active Ingredients

ACTIVE INGREDIENTS: Hydroquinone 2.00%

Ingredients

Ingredients: Water, Propylene Glycol, Mineral Oil, Stearic Acid, Palmitic Acid, Glyceryl Stearate, Cetyl Alcohol, Fragrance, Sodium Sulfite, Potassium Cetyl Phosphate, Isopropyl Myristate,
Citric Acid, Lactic Acid, Acrylates/c10-30 Alkyl Acrylate Crosspolymer, Propylparaben, Methylparaben, Brassica Campestris (Rapeseed) Seed Oil, Rosmarinus Officinalis (Rosemary) Leaf Extract. 02/10

STORAGE AND HANDLING

STORE IN A COOL, DRY PLACE - DO NOT EXPOSE TO DIRECT SUNLIGHT - ALWAYS CLOSE AFTER USE.

Use

Use: spread a thin layer on skin areas to be treated; apply mornings and evenings on perfectly cleansed skin, massaging delicately until complete absorption.

Caution

Caution: For external use only - It contains Hydroquinone - Keep away from eyes - Apply on small surfaces only - In case of allergic symptoms, immediately suspend the application - Do not use on children under 12.